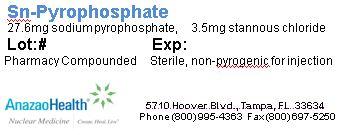 DRUG LABEL: Pyrophosphate
NDC: 51808-218 | Form: INJECTION, POWDER, LYOPHILIZED, FOR SOLUTION
Manufacturer: AnazaoHealth Corporation
Category: prescription | Type: HUMAN PRESCRIPTION DRUG LABEL
Date: 20120523

ACTIVE INGREDIENTS: SODIUM PYROPHOSPHATE 27.6 mg/1 1
INACTIVE INGREDIENTS: STANNOUS CHLORIDE 3.5 mg/1 1

Stannous Pyrophosphate

Dear Medical Professional,

Per your order, we have compounded Stannous-Pyrophosphate as a sterile lyophilized powder. The characteristics of this preparation are:

DESCRIPTION

AnazaoHealth compounds Stannous-Pyrophosphate as a sterile lyophilized powder for the preparation of Tc99m Pyrophosphate. Each 10 ml reaction vial contains: 27.6 milligrams sodium pyrophosphate decahydrate, 3.5 milligrams stannous chloride, all lyophilized under an atmosphere of nitrogen. Prior to lyophilization the pH is adjusted with hydrochloric acid. The pH of the reconstituted drug is between 4.5 and 7.5. No bacteriostatic preservative is present

INDICATIONS AND USAGE

Stannous Pyrophosphate is indicated as a blood pool imaging agent which may be used for gated pool imaging and for the detection of sites of gastrointestinal bleeding. When administered intravenously, 15-30 minutes prior to intravenous administration of sodium pertechnetate Tc99m for in vivo red blood cell labeling, approximately 75 percent of the injected activity remains in the blood pool. The modified in vivo/in vitro red blood cell labeling method may also be used for blood pool imaging.

It is also indicated as a skeletal imaging agent used to demonstrate areas of altered osteogenesis, and a cardiac imaging agent used as an adjunct in the diagnosis of acute myocardial infarction.

DOSAGE AND ADMINISTRATION

The recommended adult dose of Tc99m Pyrophosphate Injection is:

- 5 to 15 mCi for skeletal imaging
- 10 to 15 mCi for cardiac imaging
- one-third (0.33) to the entire vial contents, followed 15 to 20 mCi of sodium pertechnetate Tc 99m, for blood pool imaging

PACKAGE LABEL.PRINCIPAL DISPLAY PANEL

Figure 1